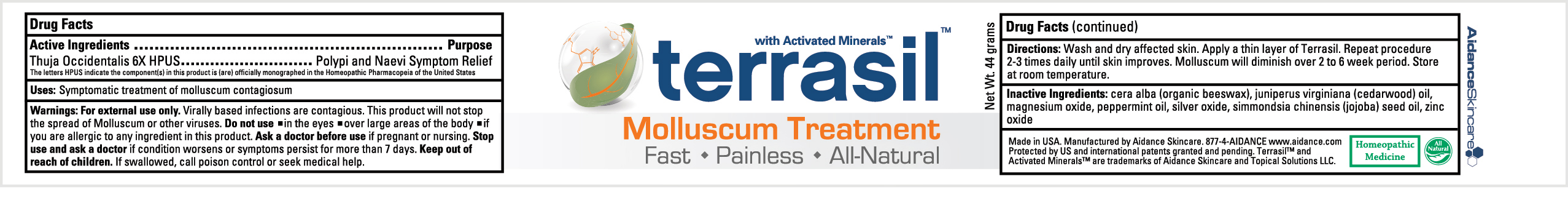 DRUG LABEL: Terrasil Molluscum Treatment
NDC: 24909-144 | Form: OINTMENT
Manufacturer: Aidance Skincare & Topical Solutions, LLC
Category: homeopathic | Type: HUMAN OTC DRUG LABEL
Date: 20121015

ACTIVE INGREDIENTS: THUJA OCCIDENTALIS LEAFY TWIG 6 [hp_X]/1 g
INACTIVE INGREDIENTS: JOJOBA OIL; JUNIPERUS VIRGINIANA OIL; MAGNESIUM OXIDE; PEPPERMINT OIL; SILVER OXIDE; WHITE WAX; ZINC OXIDE

Drug Facts

Active Ingredient

Thuja Occidentalis

The letters HPUS indicate the component(s) in this product is (are) officially monographed in the Homeopathic Pharmacopeia of the United States

Purpose

Polypi and Naevi Symptom Relief

Uses

Symptomatic treatment of molluscum contagiosum

Warnings

For external use only.
Virally based infections are contagious. This product will not stop the spread of Molluscum or other viruses.
Do not use - in the eyes - over large areas of the body - if you are allergic to any ingredient in this product.
Ask a doctor before use if pregnant or nursing.
Stop use and ask a doctor if condition worsens or symptoms persist for more than 7 days.

Keep out of reach of children.

If swallowed, call poison control or seek medical help.

Directions

Wash and dry affected skin. Apply a thin layer of Terrasil. Repeat procedure 2-3 times daily until skin improves. Molluscum will diminish over 2 to 6 week period. Store at room temperature.

Inactive Ingredients

cera alba (organic beeswax), juniperus virginiana (cedarwood) oil, silver oxide, magnesium oxide, peppermint oil, simmondsia chinensis (jojoba) seed oil, zinc oxide

PRINCIPAL DISPLAY PANEL - 44g Label

terrasil

Molluscum Treatment
Fast - Painless - All-Natural